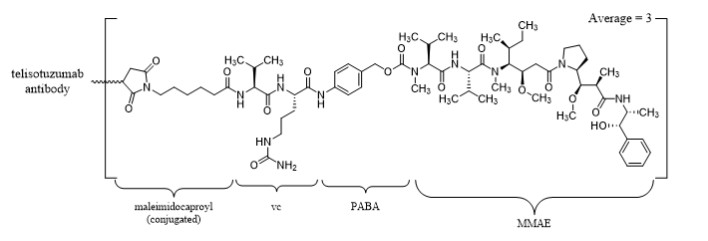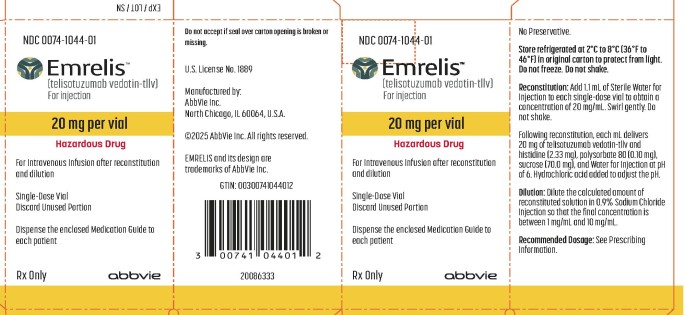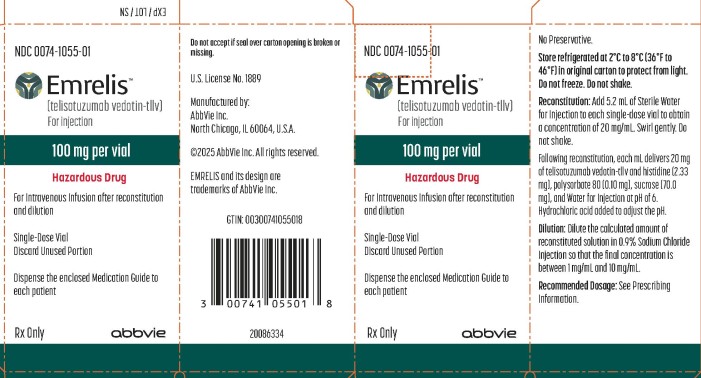 DRUG LABEL: EMRELIS
NDC: 0074-1044 | Form: INJECTION, POWDER, LYOPHILIZED, FOR SOLUTION
Manufacturer: AbbVie Inc.
Category: prescription | Type: HUMAN PRESCRIPTION DRUG LABEL
Date: 20250525

ACTIVE INGREDIENTS: TELISOTUZUMAB VEDOTIN 20 mg/1 mL
INACTIVE INGREDIENTS: HISTIDINE 2.33 mg/1 mL; POLYSORBATE 80 0.10 mg/1 mL; SUCROSE 70.0 mg/1 mL; WATER; HYDROCHLORIC ACID

HIGHLIGHTS OF PRESCRIBING INFORMATION

These highlights do not include all the information needed to use EMRELIS safely and effectively. See full prescribing information for EMRELIS.
EMRELIS™ (telisotuzumab vedotin-tllv) for injection, for intravenous use
Initial U.S. Approval: 2025

1 INDICATIONS AND USAGE

EMRELIS is a c-Met-directed antibody and microtubule inhibitor conjugate indicated for the treatment of adult patients with locally advanced or metastatic non-squamous non-small cell lung cancer (NSCLC) with high c-Met protein overexpression [≥50% of tumor cells with strong (3+) staining], as determined by an FDA-approved test, who have received a prior systemic therapy. (1)

This indication is approved under accelerated approval based on overall response rate (ORR) and duration of response (DOR). Continued approval for this indication may be contingent upon verification and description of clinical benefit in a confirmatory trial(s). (1)

2 DOSAGE AND ADMINISTRATION

For intravenous infusion only. (2.5)

- The recommended dosage of EMRELIS is 1.9 mg/kg administered intravenously every 2 weeks until disease progression or unacceptable toxicity. (2.2)
- Reconstitute and further dilute EMRELIS prior to intravenous infusion. (2.5)

3 DOSAGE FORMS AND STRENGTHS

For injection: 20 mg or 100 mg of telisotuzumab vedotin-tllv as a lyophilized powder in a single-dose vial. (3)

4 CONTRAINDICATIONS

None. (4)

5 WARNINGS AND PRECAUTIONS

- Peripheral Neuropathy: Monitor patients for new or worsening peripheral neuropathy. Withhold, reduce the dose, or permanently discontinue EMRELIS based on the severity. (5.1)
- Interstitial Lung Disease (ILD)/Pneumonitis: Severe, life-threatening or fatal ILD/pneumonitis may occur. Withhold or permanently discontinue EMRELIS based on the severity. (5.2)
- Ocular Surface Disorders: Monitor patients for signs or symptoms of ocular surface disorders, including vision changes. Withhold or permanently discontinue EMRELIS based on the severity. (5.3)
- Infusion-Related Reactions (IRR): Monitor patients for IRR. Withhold, reduce the rate of infusion, or permanently discontinue EMRELIS based on the severity. For patients who experience IRR, administer premedications prior to subsequent infusions. (5.4)
- Embryo-Fetal Toxicity: Can cause fetal harm. Advise patients about the potential risk to a fetus and to use effective contraception. (5.5)

6 ADVERSE REACTIONS

The most common adverse reactions (≥20%) were peripheral neuropathy, fatigue, decreased appetite, and peripheral edema. (6.1)

The most common Grade 3 or 4 laboratory abnormalities (≥2%) were decreased lymphocytes, increased glucose, increased alanine aminotransferase, increased gamma glutamyl transferase, decreased phosphorus, decreased sodium, decreased hemoglobin and decreased calcium. (6.1)

To report SUSPECTED ADVERSE REACTIONS, contact AbbVie Inc. at 1-800-633-9110 or FDA at 1-800-FDA-1088 or www.fda.gov/medwatch.

7 DRUG INTERACTIONS

Strong CYP3A Inhibitors: concomitant use with EMRELIS may increase the AUC of MMAE. Monitor for increased risk of adverse reactions to EMRELIS. (7.1)

8 USE IN SPECIFIC POPULATIONS

- Severe or Moderate Hepatic Impairment: Avoid use of EMRELIS. (8.6)
- Lactation: Advise not to breastfeed. (8.2)
- Infertility: May impair fertility. (8.3)

FULL PRESCRIBING INFORMATION

1 INDICATIONS AND USAGE

EMRELIS is indicated for the treatment of adult patients with locally advanced or metastatic, non-squamous non-small cell lung cancer (NSCLC) with high c-Met protein overexpression [≥50% of tumor cells with strong (3+) staining], as determined by an FDA-approved test [see Dosage and Administration (2.1)], who have received a prior systemic therapy.

This indication is approved under accelerated approval based on overall response rate (ORR) and duration of response (DOR) [see Clinical Studies (14)]. Continued approval for this indication may be contingent upon verification and description of clinical benefit in a confirmatory trial(s).

2 DOSAGE AND ADMINISTRATION

2.1 Patient Selection

Select patients for treatment with EMRELIS based on the presence of high c-Met protein overexpression [≥50% of tumor cells with strong (3+) staining] in patients with non-squamous NSCLC [see Indications and Usage (1) and Clinical Studies (14)].

Information on FDA-approved tests for the detection of high c-Met protein overexpression is available at: http://www.fda.gov/CompanionDiagnostics.

2.2 Recommended Dosage

The recommended dosage of EMRELIS is 1.9 mg/kg (up to a maximum of 190 mg for patients greater than or equal to 100 kg) administered as an intravenous infusion over 30 minutes every 2 weeks until disease progression or unacceptable toxicity.

2.3 Dosage Modifications for Adverse Reactions

The recommended dose reductions for adverse reactions are provided in Table 1.

Table 1. Recommended Dose Reductions
Dose Reduction | Recommended Dosage
First | 1.6 mg/kg every 2 weeks
Second | 1.3 mg/kg every 2 weeks
Third | 1 mg/kg every 2 weeks
Permanently discontinue EMRELIS in patients who are unable to tolerate 1 mg/kg.

The recommended dosage modifications of EMRELIS for adverse reactions are provided in Table 2.

Table 2. EMRELIS Dosage Modifications and Management for Adverse Reactions
Adverse Reaction | Severitya | Dosage Modification
Peripheral Neuropathy [see Warnings and Precautions (5.1)] | Grade 2 or 3 | - Withhold EMRELIS until recovery to Grade ≤1. - Resume EMRELIS at the next lower dose level.
 | Grade 4 | Permanently discontinue EMRELIS.
Interstitial Lung Disease (ILD)/Pneumonitis [see Warnings and Precautions (5.2)] | Grade 1 | - Withhold EMRELIS and consider corticosteroids as soon as ILD/pneumonitis is suspected. - Resume EMRELIS upon radiographic resolution.
 | Grade ≥2 | Permanently discontinue EMRELIS.
Keratitis [see Warnings and Precautions (5.3)] | Grade 2 | - Withhold EMRELIS. - Refer patients to an eye care professional for an ophthalmic examination and treatment (e.g., lubricating and/or steroidal eye drops). - Resume EMRELIS at the same dose at the discretion of the healthcare provider.
 | Grade 3 or 4 | - Refer patients to an eye care professional for an ophthalmic examination and treatment (e.g., lubricating and/or steroidal eye drops). - Permanently discontinue EMRELIS.
Infusion-Related Reactions (IRR) [see Warnings and Precautions (5.4)] | Grade 1-3 | - Interrupt EMRELIS infusion and administer supportive treatment. - Resume the infusion at a 50% rate reduction. Increase infusion rate as tolerated for subsequent doses. - For patients who experience an IRR, administer premedications prior to all future doses (see Table 3).
 | Grade 4 | - Permanently discontinue EMRELIS. - Administer supportive treatment.
Peripheral Edema [see Adverse Reactions (6.1)] | Grade ≥2 | First occurrence; - Withhold EMRELIS until recovery to Grade ≤1. - Resume EMRELIS at the same dose level.; Subsequent occurrence; - Withhold EMRELIS until recovery to Grade ≤1. - Resume EMRELIS at the next lower dose level.
Other Adverse Reactions [see Adverse Reactions (6.1)] | Grade 3 | First occurrence; - Withhold EMRELIS until recovery to Grade ≤1. - Resume EMRELIS at the same dose.; Subsequent occurrence; - Withhold EMRELIS until recovery to Grade ≤1. - Resume EMRELIS at the next lower dose level.
 | Grade 4 | - Permanently discontinue EMRELIS.
aAdverse reactions were graded using National Cancer Institute Common Terminology Criteria for Adverse Events (NCI CTCAE) version 4.03

2.4 Recommended Premedications for Patients Who Experience Infusion-Related Reactions

Table 3 contains the recommended premedications for patients who experience infusion-related reactions to EMRELIS, for subsequent infusions.

Table 3: Recommended Premedications for Patients Who Experience Infusion-Related Reactions
Medication Class | Examples or equivalent | Dose | Route of Administration | Dosing Window Prior to EMRELIS Administration
H1 Antihistamine | Diphenhydramine | 25 to 50 mg | Intravenously or orally | Administer 30-60 minutes prior to each infusion
H2 Antihistamine | Famotidine | 20 mg | Intravenously or orally | Administer 30-60 minutes prior to each infusion
Antipyretic | Acetaminophen | 650 to 1,000 mg | Intravenously or orally | Administer 30-60 minutes prior to each infusion
Glucocorticoid | Methylprednisolone | 125 mg or equivalent | Intravenously | Administer 30-60 minutes prior to each infusion

2.5 Preparation and Administration

EMRELIS contains a hazardous component. Follow applicable special handling and disposal procedures in accordance with local requirements.^1

Reconstitute and further dilute EMRELIS prior to intravenous infusion.

Reconstitution of Lyophilized EMRELIS

Before reconstitution, allow the vial to reach room temperature after removal of the vial from storage condition.

- Calculate the recommended dose based on the patient’s weight to determine the number of vials needed. For patients weighing greater than or equal to 100 kg, use 190 mg dose [see Dosage and Administration (2.2)]. More than one vial may be needed to achieve the calculated dose.
- Using a sterile syringe, slowly inject Sterile Water for Injection, using the volume provided in Table 4, into the EMRELIS vial containing the lyophilized powder, which has a whole or fragmented cake-like appearance. The reconstituted solution has a concentration of 20 mg/mL EMRELIS.

Table 4. Reconstitution Volumes
Dose Vial | Volume of Sterile Water for Injection required for reconstitution
20 mg vial | 1.1 mL
100 mg vial | 5.2 mL

- Swirl the vial gently until completely dissolved. Do not shake.
- Inspect the reconstituted solution for particulate matter and discoloration. The solution should appear clear to slightly opalescent and colorless to slightly yellow. Discard the vial if the reconstituted solution is discolored, is cloudy, or contains visible particulates.
- Use reconstituted EMRELIS immediately. If not used immediately, store the reconstituted EMRELIS vials in a refrigerator at 2°C to 8°C (36°F to 46°F) for up to 24 hours from the time of reconstitution. Do not freeze.
- Each vial of EMRELIS is intended for one-time use only. Discard any unused drug remaining in the vial.

Dilution in Infusion Bag

- Calculate the required dose volume (mL) of reconstituted EMRELIS solution based on the prescribed dose.
- Withdraw the calculated dose volume (mL) of reconstituted solution from the EMRELIS vial using a sterile syringe. Discard any unused portion remaining in the vial(s).
- Inject the calculated amount of reconstituted solution into 0.9% Sodium Chloride Injection infusion bag so that the final EMRELIS concentration is between 1 mg/mL and 10 mg/mL. Use only 0.9% Sodium Chloride Injection.
- Gently invert the infusion bag to thoroughly mix the solution. Do not shake.
- After preparing the dose for infusion, visually inspect the bag content for particulates and discard if present.
- If not used immediately, the diluted solution can be stored in a refrigerator at 2°C to 8°C (36°F to 46°F) for up to 24 hours and an additional 4 hours at room temperature at 9°C to 30°C (48°F to 86°F) until the end of administration. Do not freeze.

Method of Administration

If the prepared infusion solution was stored refrigerated at 2°C to 8°C (36°F to 46°F), allow the solution to reach room temperature prior to administration.

- Administer by intravenous infusion over 30 minutes using a dedicated infusion line with a 0.20 or 0.22 micron in-line filter made of polyether sulfone (PES), polyvinylidene fluoride (PVDF), or Polyamide (PA).
- Do not mix EMRELIS with other drugs or administer other drugs through the same intravenous line.

3 DOSAGE FORMS AND STRENGTHS

For injection: 20 mg or 100 mg of telisotuzumab vedotin-tllv as a white to off-white, lyophilized powder in a single-dose vial for reconstitution and further dilution.

4 CONTRAINDICATIONS

None.

5 WARNINGS AND PRECAUTIONS

5.1 Peripheral Neuropathy

EMRELIS can cause peripheral neuropathy, including peripheral sensory neuropathy and peripheral motor neuropathy.

In the safety population [see Adverse Reactions (6.1)], peripheral neuropathy occurred in 51% of patients treated with EMRELIS, including Grade 3 in 11%. These adverse reactions included peripheral sensory neuropathy in 45% of patients and peripheral motor neuropathy in 9%. The median time to onset of peripheral neuropathy was 105 days (range: 1 to 472 days). Peripheral neuropathy led to permanent discontinuation of EMRELIS in 13% of patients. The median time to onset of peripheral neuropathy leading to treatment discontinuation was 249 days (range: 57 to 519 days). Of the 7 patients with motor neuropathy ongoing as of their last dose of EMRELIS, 6 had persistent Grade 1 or 2 symptoms 30 days after their last dose.

Monitor patients for signs and symptoms of new or worsening peripheral neuropathy such as hypoesthesia, hyperesthesia, paresthesia, a burning sensation, neuropathic pain, or muscle weakness. Withhold, reduce the dose or permanently discontinue EMRELIS based on severity [see Dosage and Administration (2.3)].

5.2 Interstitial Lung Disease/Pneumonitis

EMRELIS can cause severe, life-threatening, or fatal interstitial lung disease (ILD)/pneumonitis.

In the safety population [see Adverse Reactions (6.1)], ILD/pneumonitis occurred in 10% of patients treated with EMRELIS, including Grade 3 in 3% and Grade 4 in 0.6%. There were 3 fatal cases of ILD/pneumonitis in patients who received EMRELIS. The median time to onset of ILD/pneumonitis was 48 days (range: 23 to 85 days). ILD/pneumonitis led to permanent discontinuation of EMRELIS in 7% of patients. The median time to onset of ILD/pneumonitis leading to treatment discontinuation was 46 days (range: 23 to 85 days).

Advise patients to immediately report cough, dyspnea, fever, and/or any new or worsening respiratory symptoms. Monitor patients for signs and symptoms of ILD/pneumonitis. Withhold or permanently discontinue EMRELIS based on severity [see Dosage and Administration (2.3)].

5.3 Ocular Surface Disorders

EMRELIS can cause ocular surface disorders including blurred vision, visual impairment, keratitis, and dry eye.

In the safety population [see Adverse Reactions (6.1)], ocular surface disorders occurred in 25% of patients treated with EMRELIS. The most common ocular surface disorders were blurred vision (15%), keratitis (11%), and dry eye (5%). Grade 3 ocular surface disorders occurred in 1.2% of patients [blurred vision (1.2%), and keratitis (0.6%)]. The median time to onset of ocular surface disorders was 47 days (range: 1 to 319 days).

Monitor patients for ocular surface disorders during treatment with EMRELIS. Withhold EMRELIS and refer patients to an eye care professional for an ophthalmic examination and treatment for patients who develop Grade ≥2 ocular toxicity. Withhold or permanently discontinue EMRELIS based on severity [see Dosage and Administration (2.3)].

5.4 Infusion-Related Reactions

EMRELIS can cause infusion-related reactions (IRR); signs and symptoms of IRR include dyspnea, flushing, chills, nausea, chest discomfort, and hypotension. The median time to onset of IRR was 28 days (range: 1 to 43 days).

In the safety population, [see Adverse Reactions (6.1)], IRR occurred in 3% of patients treated with EMRELIS including Grade 3 in 1.2% and Grade 4 in 0.6%. IRR led to permanent discontinuation of EMRELIS in 0.6% of patients.

Monitor patients for signs and symptoms of infusion reactions during EMRELIS infusion. Withhold, reduce the rate of infusion, or permanently discontinue EMRELIS based on severity [see Dosage and Administration (2.3)]. For patients who experience IRR, administer premedications prior to subsequent infusions.

5.5 Embryo-Fetal Toxicity

Based on the mechanism of action and findings in animals, EMRELIS can cause fetal harm when administered to a pregnant woman. The small molecule component of EMRELIS, MMAE, administered to rats caused adverse developmental outcomes, including embryo-fetal mortality and structural abnormalities, at exposures similar to those occurring clinically at the recommended dose.

Advise patients of the potential risk to a fetus. Advise females of reproductive potential to use effective contraception during treatment with EMRELIS and for 2 months after the last dose. Advise male patients with female partners of reproductive potential to use effective contraception during treatment with EMRELIS and for 4 months after the last dose [see Use in Specific Populations (8.1, 8.3) and Clinical Pharmacology (12.1)].

6 ADVERSE REACTIONS

The following clinically significant adverse reactions are described elsewhere in the labeling:

- Peripheral Neuropathy [see Warnings and Precautions (5.1)]
- Interstitial Lung Disease (ILD)/Pneumonitis [see Warnings and Precautions (5.2)]
- Ocular Surface Disorders [see Warnings and Precautions (5.3)]
- Infusion-Related Reactions (IRR) [see Warnings and Precautions (5.4)]

6.1 Clinical Trials Experience

Because clinical studies are conducted under widely varying conditions, adverse reaction rates observed in the clinical studies of a drug cannot be directly compared to rates in the clinical studies of another drug and may not reflect the rates observed in practice.

LUMINOSITY

The safety population described in WARNINGS AND PRECAUTIONS and below reflects exposure to EMRELIS in 168 patients with locally advanced or metastatic EGFR wild-type non-squamous NSCLC with c-Met protein overexpression who received EMRELIS as a single agent administered at 1.9 mg/kg intravenously every 2 weeks in the LUMINOSITY study [see Clinical Studies (14)]. Among patients who received EMRELIS, 42% were exposed for 6 months or longer and 11% were exposed for greater than one year.

The median age of patients who received EMRELIS was 64.5 years (range: 33 to 83 years); 70% were male; 65% were White; 1.8% were Black or African American, 33% were Asian; and 0.6% were of Hispanic or Latino ethnicity.

Serious adverse reactions occurred in 35% of patients. Serious adverse reactions occurring in ≥2% of patients included ILD/pneumonitis (5%), pneumonia (5%), peripheral neuropathy (3.6%), and pleural effusion (2.4%). Fatal adverse reactions occurred in 5% of patients who received EMRELIS, including ILD/pneumonitis (1.8%), pneumonia (1.2%), sudden death (1.2%), noninfectious endocarditis (0.6%) and myocardial infarction (0.6%).

Permanent discontinuations of EMRELIS due to adverse reactions occurred in 30% of patients. Adverse reactions which resulted in permanent discontinuation of EMRELIS in ≥2% included peripheral neuropathy and ILD/pneumonitis.

Dosage interruptions due to adverse reactions occurred in 44% of patients. Adverse reactions which required dosage interruption in ≥2% of patients included peripheral neuropathy, fatigue, pneumonia, increased ALT, blurred vision, COVID-19, ILD/pneumonitis, and keratitis.

Dose reductions due to adverse reactions occurred in 28% of patients. Adverse reactions which required dose reductions in ≥2% of patients included peripheral neuropathy, fatigue, and keratitis.

The most common adverse reactions (≥20%) were peripheral neuropathy, fatigue, decreased appetite, and peripheral edema.

The most common Grade 3 or 4 laboratory abnormalities (≥2%) were decreased lymphocytes, increased glucose, increased ALT, increased gamma glutamyl transferase, decreased phosphorus, decreased sodium, decreased hemoglobin and decreased calcium.

Table 5 summarizes the adverse reactions in LUMINOSITY.

Table 5. Adverse Reactions (≥10%) in Patients with EGFR Wild-Type Non-squamous NSCLC with c-Met Protein Overexpression in LUMINOSITY
Adverse Reaction | EMRELIS (N=168)
 | All Grades^1 % | Grade 3 or 4^1 %
Nervous system disorders
Peripheral neuropathy^2 | 51 | 11
General disorders and administration site conditions
Fatigue^2 | 29 | 3.6
Peripheral edema^2 | 22 | 1.8
Metabolism and nutrition disorders
Decreased appetite | 22 | 0.6
Gastrointestinal disorders
Nausea | 15 | 0
Constipation | 14 | 0.6
Vomiting | 10 | 0.6
Eye disorders
Blurred vision^3 | 15 | 1.2
Keratitis^4 | 11 | 0.6
Infections and infestations
Pneumonia^2 | 13 | 6
Respiratory, thoracic and mediastinal disorders
ILD/pneumonitis^2 | 10 | 3.6
^1Events were graded using NCI CTCAE version 4.03.
^2Grouped term.
^3Includes vision blurred, visual acuity reduced, visual impairment.
^4Includes corneal cyst, corneal disorder, corneal erosion, corneal edema, corneal opacity, keratitis, keratitis interstitial, punctate keratitis.

Other clinically relevant adverse reactions in <10% of patients who received EMRELIS included arthralgia, dizziness, dry eye, infusion-related reaction and photophobia.

Table 6 presents laboratory abnormalities in LUMINOSITY.

Table 6. Select Laboratory Abnormalities (≥10%) that Worsened from Baseline in Patients with EGFR Wild-Type Non-squamous NSCLC with c-Met Protein Overexpression in LUMINOSITY
Laboratory Abnormality | EMRELIS (N=168)
 | All Grades % | Grade 3 or 4 %
Chemistry
Albumin decreased | 61 | 0.6
Glucose increased | 58 | 4.8
Calcium decreased | 47 | 2.4
Alanine transaminase increased | 41 | 4.8
Gamma glutamyl transferase increased | 36 | 4.3
Aspartate aminotransferase increased | 34 | 0.6
Phosphorus decreased | 33 | 4.2
Sodium decreased | 30 | 3.6
Alkaline phosphatase increased | 30 | 0.6
Creatinine increased | 16 | 1.2
Potassium decreased | 14 | 1.2
Magnesium decreased | 14 | 0.6
Glucose decreased | 11 | 0
Magnesium increased | 10 | 0
Hematology
Lymphocytes decreased | 37 | 10
Hemoglobin decreased | 35 | 3.6
White blood cells decreased | 16 | 1.2
Platelets decreased | 14 | 0.6
Neutrophils decreased | 10 | 1.2

Percentages were calculated using patients with worsening laboratory values from baseline and the number of patients with both baseline and post-treatment measurements as the denominator.

7 DRUG INTERACTIONS

7.1 Effect of Other Drugs on EMRELIS

Strong CYP3A Inhibitors

Concomitant use with strong CYP3A inhibitors may increase unconjugated MMAE AUC [see Clinical Pharmacology (12.3)], which may increase the risk of EMRELIS adverse reactions. Monitor patients for adverse reactions when EMRELIS is given concomitantly with strong CYP3A inhibitors.

8 USE IN SPECIFIC POPULATIONS

8.1 Pregnancy

Risk Summary

Based on the mechanism of action and findings in animals, EMRELIS can cause fetal harm when administered to a pregnant woman [see Clinical Pharmacology (12.1)]. There are no available human data on EMRELIS use in pregnant women to inform a drug-associated risk. In an animal reproduction study, administration of the small molecule component of EMRELIS, MMAE, to pregnant rats during organogenesis resulted in embryo-fetal mortality and structural abnormalities at exposures similar to the clinical exposure at the recommended dose [see Data]. Advise patients of the potential risks to a fetus.

In the U.S. general population, the estimated background risk of major birth defects and miscarriage in clinically recognized pregnancies is 2% to 4% and 15% to 20%, respectively.

Data

Animal Data

No embryo-fetal development studies in animals have been performed with telisotuzumab vedotin-tllv. In an embryo-fetal development study in pregnant rats, administration of two intravenous doses of MMAE, the small molecule component of EMRELIS, on gestational days 6 and 13 caused embryo-fetal mortality and structural abnormalities, including protruding tongue, agnathia, malrotated limbs, and gastroschisis compared to controls at a dose of 0.2 mg/kg (approximately 2 times the human area under the curve [AUC] at the recommended dose).

8.2 Lactation

Risk Summary

There are no data on the presence of telisotuzumab vedotin-tllv or MMAE in human milk, the effects on the breastfed child, or the effects on milk production. Because of the potential for serious adverse reactions in a breastfed child, advise lactating women not to breastfeed during treatment with EMRELIS and for 1 month after the last dose.

8.3 Females and Males of Reproductive Potential

EMRELIS can cause fetal harm when administered to a pregnant woman [see Use in Specific Populations (8.1)].

Pregnancy Testing

Verify pregnancy status in females of reproductive potential prior to initiating EMRELIS treatment.

Contraception

Females

Advise females of reproductive potential to use effective contraception during treatment with EMRELIS and for 2 months after the last dose.

Males

Based on genotoxicity findings, advise male patients with female partners of reproductive potential to use effective contraception during treatment with EMRELIS and for 4 months after the last dose.

Infertility

Females

Based on findings in animal studies with MMAE-containing antibody-drug conjugates (ADCs), EMRELIS may impair female fertility. The effect on fertility is reversible [see Nonclinical Toxicology (13.1)].

Males

Based on findings from animal studies, EMRELIS may impair male fertility. The reversibility of this effect is unknown [see Nonclinical Toxicology (13.1)].

8.4 Pediatric Use

Safety and effectiveness of EMRELIS have not been established in pediatric patients.

8.5 Geriatric Use

Of the 168 patients with previously treated EGFR wild-type non-squamous NSCLC with c-Met protein overexpression treated with EMRELIS in LUMINOSITY, 50% were ≥65 years of age and 12% were ≥75 years of age. No overall differences in safety or effectiveness were observed between older and younger patients.

8.6 Hepatic Impairment

Avoid use of EMRELIS in patients with moderate or severe hepatic impairment (total bilirubin >1.5 x ULN and any AST).

Patients with moderate or severe hepatic impairment are likely to have increased exposure to MMAE, which may increase the risk of adverse reactions. EMRELIS has not been studied in patients with moderate or severe hepatic impairment.

No dosage adjustment is recommended for patients with mild hepatic impairment (total bilirubin ≤ULN and AST >ULN or total bilirubin >ULN and ≤1.5 x ULN and any AST) [see Clinical Pharmacology (12.3)].

11 DESCRIPTION

Telisotuzumab vedotin-tllv is a c-Met directed antibody-drug conjugate (ADC) comprised of a humanized immunoglobulin G1 kappa (IgG1κ) monoclonal antibody conjugated to the small molecule microtubule-disrupting agent, monomethyl auristatin E (MMAE), via a protease-cleavable valine-citrulline (vc) linker. The antibody is produced in a mammalian cell line (Chinese hamster ovary) and the drug-linker is produced by chemical synthesis. Each monoclonal antibody molecule carries an average of 3 MMAE molecules. Telisotuzumab vedotin-tllv has an approximate molecular weight of 152 kDa.

EMRELIS (telisotuzumab vedotin-tllv) for injection is a sterile, white to off-white, preservative-free, lyophilized powder in a single-dose vial for reconstitution and dilution prior to intravenous infusion. EMRELIS is supplied as 20 mg per vial or 100 mg per vial and requires reconstitution with Sterile Water for Injection, USP (1.1 mL and 5.2 mL, respectively) to obtain a concentration of 20 mg/mL [see Dosage and Administration (2.4)]. Following reconstitution, each mL delivers 20 mg of telisotuzumab vedotin-tllv, and histidine (2.33 mg), polysorbate 80 (0.10 mg), sucrose (70.0 mg), and Water for Injection. Hydrochloric acid was added to adjust the pH to 6.0.

12 CLINICAL PHARMACOLOGY

12.1 Mechanism of Action

Telisotuzumab vedotin-tllv is a c-Met-directed antibody drug conjugate (ADC). The antibody is a humanized IgG1κ directed against c-Met, the cell surface receptor for hepatocyte growth factor. The small molecule, MMAE, is a microtubule-disrupting agent, attached to the antibody via a protease cleavable linker. Following binding to c-Met-expressing cells, telisotuzumab vedotin-tllv undergoes internalization and intracellular cleavage of MMAE. MMAE disrupts the microtubule network of actively dividing cells, subsequently inducing cell cycle arrest and apoptotic cell death. Telisotuzumab vedotin-tllv exhibited antitumor activity in xenograft models of NSCLC.

12.2 Pharmacodynamics

Exposure Response Relationships

Exposure-response relationships for efficacy and time course of pharmacodynamic response have not been fully characterized.

Higher telisotuzumab vedotin-tllv exposure was associated with increased rates of Grade 3 peripheral neuropathy, and Grades 2 and 3 ocular surface disorders. Higher unconjugated MMAE exposure was associated with increased rates of Grade ≥3 adverse reactions and fatal adverse reactions.

Cardiac Electrophysiology

There is insufficient information to characterize the effect of telisotuzumab vedotin-tllv on the QT interval.

12.3 Pharmacokinetics

The exposure parameters of telisotuzumab vedotin-tllv (ADC) and unconjugated MMAE (cytotoxic component of EMRELIS) are summarized in Table 7. The plasma exposure of the ADC and unconjugated MMAE increased proportionally over a dose range of 1.2 to 3.3 mg/kg (0.64 to 1.7 times the approved recommended dose). ADC time to maximum plasma concentrations (Tmax) occurs at the end of intravenous infusion while MMAE Tmax occurs approximately 5 days after EMRELIS administration. Minimal accumulation of the ADC or MMAE occurs.

Table 7. Exposure Parameters of Telisotuzumab Vedotin-tllv (ADC) and Unconjugated MMAE at EMRELIS 1.9 mg/kg Every 2 Weeks
 | ADC | Unconjugated MMAE
Cmax | 29 (43) µg/mL | 2.2 (53) ng/mL
AUC0-tau | 2,130 (55) µg∙hr/mL | 405 (64) ng∙hr/mL

Cmax = maximum concentration

AUC0-tau = area under the concentration-time curve from time zero to 14 days (2 weeks)

Distribution

The estimated volume of distribution is 3.4 L (16.5%CV) for telisotuzumab vedotin-tllv.

MMAE plasma protein binding ranges from 68% to 82% in vitro.

Elimination

The elimination half-life is approximately 3 days for the ADC and approximately 4 days for MMAE. The estimated clearance (CL) is 1.3 L/day (31.5%CV) for the ADC and 76 L/day (52.1%CV) for MMAE.

Metabolism

Telisotuzumab vedotin-tllv catabolism has not been studied in humans; however, it is expected to undergo catabolism to small peptides, amino acids, unconjugated MMAE, and unconjugated MMAE-related catabolites. MMAE is metabolized primarily by CYP3A4.

Specific Populations

No clinically significant differences in the pharmacokinetics of the ADC or unconjugated MMAE were observed based on age (30 to 87 years), sex, race (65% White, 32% Asian, and 3% Black), body weight (34 to 144 kg), mild or moderate renal impairment (CLcr 30 to 89 mL/min, estimated by Cockcroft-Gault), or mild hepatic impairment (total bilirubin ≤ULN and AST >ULN or total bilirubin >ULN and ≤1.5 x ULN and any AST).

The effect of severe renal impairment (CLcr <30 mL/min), end-stage renal disease with or without dialysis, or moderate to severe hepatic impairment (total bilirubin >1.5 × ULN and any AST) on the pharmacokinetics of telisotuzumab vedotin-tllv or unconjugated MMAE is unknown.

Drug Interaction Studies

Clinical Studies and Model-Informed Approaches:

No clinical studies have evaluated the potential for drug-drug interactions.

Strong CYP3A4 Inhibitor:

MMAE AUC is predicted to increase by 1.4-fold following concomitant administration of EMRELIS with ketoconazole (a strong CYP3A inhibitor).

Strong CYP3A4 Inducer:

MMAE AUC is predicted to decrease by 70% following concomitant administration of EMRELIS with rifampicin (a strong CYP3A inducer).

Sensitive CYP3A Substrate:

No clinically significant difference in the pharmacokinetics of midazolam (a sensitive CYP3A substrate) is predicted when used concomitantly with EMRELIS.

In Vitro Studies

Cytochrome P450 (CYP) Enzymes:

MMAE is a substrate and an inhibitor of CYP3A4/5.

Transporter Systems:

MMAE is a substrate of P-glycoprotein (P-gp).

12.6 Immunogenicity

The observed incidence of anti-drug antibodies is highly dependent on the sensitivity and specificity of the assay. Differences in assay methods preclude meaningful comparisons of the incidence of anti-drug antibodies in the study described below with the incidence of anti-drug antibodies in other studies, including those of EMRELIS or of other telisotuzumab products.

Following administration of EMRELIS in LUMINOSITY, 22% (60/269) of patients tested positive for treatment-emergent antibodies against telisotuzumab vedotin-tllv at one or more post-baseline time points. Of those who tested positive for anti-drug antibody, neutralizing antibodies were detected in 38% (23/60) of patients. Development of anti-drug antibodies and neutralizing antibodies resulted in a 17% decrease in clearance of telisotuzumab vedotin-tllv. There are insufficient data to assess whether the observed anti-telisotuzumab vedotin-tllv antibody-associated pharmacokinetic changes affect the safety and effectiveness of EMRELIS.

13 NONCLINICAL TOXICOLOGY

13.1 Carcinogenesis, Mutagenesis, Impairment of Fertility

Carcinogenesis

Carcinogenicity studies in animals have not been performed with telisotuzumab vedotin-tllv or the small molecule MMAE.

Mutagenesis

MMAE was positive for genotoxicity in the in vivo rat bone marrow micronucleus study through an aneugenic mechanism. MMAE was not mutagenic in the bacterial reverse mutation (Ames) assay or the L5178Y TK+/- mouse lymphoma forward mutation assay.

Impairment of Fertility

Fertility studies with telisotuzumab vedotin-tllv or MMAE have not been conducted. However, results of repeat-dose toxicity studies in rats and monkeys indicate the potential for telisotuzumab vedotin-tllv to impair male and female reproductive function and fertility.

In a 2-week repeat-dose toxicology study in rats, telisotuzumab vedotin-tllv administered at doses ≥6 mg/kg (≥12 times the human exposure [AUC] at the recommended dose) resulted in decreased number/degeneration of germ cells in the testes largely due to loss of spermatogonia. The reversibility of these findings was not assessed.

In a 4-week repeat-dose toxicology study in sexually immature monkeys, telisotuzumab vedotin-tllv administered at doses ≥3 mg/kg (≥4 times the human exposure [AUC] at the recommended dose) resulted in degeneration of granulosa cells and decreased number of tertiary follicles in the ovaries and degeneration/necrosis of endometrial glands in the uterus. There was evidence of reversibility after an 8-week recovery period.

14 CLINICAL STUDIES

Previously Treated EGFR Wild-Type Non-squamous NSCLC with High c-Met Protein Overexpression

LUMINOSITY

The efficacy of EMRELIS was evaluated in the LUMINOSITY study (NCT03539536), a multicenter, open-label, single-arm, multi-cohort clinical trial. Eligible patients were required to have locally advanced or metastatic NSCLC with c-Met protein overexpression and treatment with prior systemic therapy (including no more than one line of prior chemotherapy) in the locally advanced or metastatic setting. The study excluded patients who had received radiation therapy to the lungs <6 months prior to enrollment and patients who had a history of ILD/pneumonitis requiring treatment with steroids or ILD/pneumonitis within 3 months of the first dose.

Patients received EMRELIS at 1.9 mg/kg intravenously every 2 weeks until disease progression or unacceptable toxicity. The major efficacy outcome measure was overall response rate (ORR) according to Response Evaluation Criteria in Solid Tumors (RECIST) version 1.1 as assessed by a blinded independent central review (BICR). An additional efficacy outcome measure was duration of response (DOR) by BICR.

The efficacy population included 84 patients with non-squamous, EGFR wild-type NSCLC with high c-Met protein overexpression who had received prior systemic therapy. High c-Met protein overexpression was defined as ≥50% of tumor cells with strong (3+) membrane staining on archival or recent tissue samples by immunohistochemistry (IHC) and was determined by prospective testing at a central laboratory prior to enrollment using the MET (SP44) clinical trial assay (CTA). Of the 84 patients with high c-Met protein overexpression identified by central testing using the CTA, tissue samples from 38/84 (45%) patients were tested retrospectively using the VENTANA MET (SP44) RxDx assay. One sample was unevaluable. Of the 37 samples retested and evaluable, 32 (87%) samples were confirmed to have high c-Met protein overexpression, defined as ≥50% of tumor cells with strong (3+) membrane and/or cytoplasmic staining.

The median age was 64 years (range: 38 to 83 years); 75% were male; 61% were White, 1.2% were Black or African American, 38% were Asian; none were of Hispanic or Latino ethnicity. Twenty-five percent had an Eastern Cooperative Oncology Group Performance Status (ECOG PS) of 0 and 74% had ECOG PS of 1; 19% were never smokers, 68% were former smokers, and 13% were current smokers; 99% had Stage IV disease; and 19% of patients had previously treated brain metastases. The median number of lines of prior therapies was 1 (range 1 - 3); 73% of patients had one line, 24% had two lines, and 3.6% had three lines of prior systemic therapy; 96% of patients had prior platinum therapy, 82% had prior immunotherapy (anti-PD-1/PD-L1), 6% had prior targeted therapy, and 3.6% had prior MET tyrosine kinase inhibitor therapy.

Efficacy results are summarized in Table 8.

Table 8. Efficacy Results in LUMINOSITY for Patients with EGFR Wild-Type Non-squamous NSCLC with High c-Met Protein Overexpression
Efficacy Parameter | EMRELIS N = 84
Confirmed Overall Response Rate (ORR), % (95% CI) | 35 (24, 46)
Complete Response, % | 0
Partial Response, % | 35
Duration of Response | N = 29
Median, months (95% CI) | 7.2 (4.2, 12)
DOR ≥6 months,a % | 59
DOR ≥12 months,a % | 21
CI=confidence interval; DOR=duration of response
a Based on observed duration of response in 29 responders.

15 REFERENCES

1. "OSHA Hazardous Drugs." OSHA. http://www.osha.gov/SLTC/hazardousdrugs/index.html

16 HOW SUPPLIED/STORAGE AND HANDLING

How Supplied

EMRELIS (telisotuzumab vedotin-tllv) for injection is a sterile, preservative-free, white to off-white lyophilized powder, supplied in a glass single-dose vial.

- Carton of one 20 mg/vial (NDC 0074-1044-01)
- Carton of one 100 mg/vial (NDC 0074-1055-01)

Storage and Handling

Store refrigerated at 2oC to 8oC (36oF to 46oF) in original carton to protect from light. Do not freeze. Do not shake.

Special Handling

EMRELIS is a hazardous product. Follow special handling and disposal procedures.^1

17 PATIENT COUNSELING INFORMATION

Advise the patient to read the FDA-approved patient labeling (Medication Guide).

Peripheral Neuropathy

Advise patients that EMRELIS can cause peripheral neuropathy. Advise patients to report to their healthcare provider any new or worsening numbness or tingling of the hands or feet or any muscle weakness [see Warnings and Precautions (5.1)].

ILD/Pneumonitis

Advise patients that EMRELIS can cause ILD/pneumonitis. Advise patients to immediately report to their healthcare provider any new or worsening respiratory symptoms [see Warnings and Precautions (5.2)].

Ocular Surface Disorders

Advise patients that EMRELIS can cause ocular surface disorders. Advise patients to contact their healthcare provider any new or worsening ocular problems or vision changes [see Warnings and Precautions (5.3)].

Infusion-Related Reactions

Advise patients that EMRELIS can cause infusion-related reactions. Advise patients to immediately contact their healthcare provider if they experience signs and symptoms of infusion reactions, including fever, chills, rash, or breathing problems [see Warnings and Precautions (5.4)].

Embryo-Fetal Toxicity

Advise pregnant women and females of reproductive potential of the potential risk to a fetus. Advise female patients to contact their healthcare provider if they become pregnant, or if pregnancy is suspected, during treatment with EMRELIS [see Warnings and Precautions (5.5) and Use in Specific Populations (8.1)].

Females and Males of Reproductive Potential

- Advise females of reproductive potential to use effective contraception during treatment and for 2 months after the last dose [see Use in Specific Populations (8.3)].
- Advise male patients with female partners of reproductive potential to use effective contraception during treatment and for 4 months after the last dose [see Use in Specific Populations (8.3)].

Lactation

Advise women not to breastfeed during treatment with EMRELIS and for 1 month after the last dose [see Use in Specific Populations (8.2)].

Infertility

Advise males and females of reproductive potential that EMRELIS may impair fertility [see Nonclinical Toxicology (13)].

EMRELIS™ [telisotuzumab vedotin-tllv]

Manufactured by:
AbbVie Inc.
North Chicago, IL 60064, U.S.A.
U.S. License No. 1889
© 2025 AbbVie. All rights reserved.
EMRELIS and its design are trademarks of AbbVie Inc.

20090524

MEDICATION GUIDE
EMRELIS™ (EM-rell-is)
(telisotuzumab vedotin-tllv)
for injection, for intravenous use

What is the most important information I should know about EMRELIS?
EMRELIS can cause serious side effects, including:

- Nerve problems in your hands or feet (peripheral neuropathy). Nerve problems are common during treatment with EMRELIS and can also be severe. Tell your healthcare provider if you develop any new or worsening signs or symptoms of nerve problems, including:

- numbness
- tingling
- burning sensation

- pain or discomfort
- muscle weakness
- difficulty walking

- Lung problems. EMRELIS can cause lung problems that may be severe, life-threatening or that may lead to death. Tell your healthcare provider right away if you develop new or worsening lung symptoms, including:

- cough
- trouble breathing or shortness of breath

- fever
- wheezing

- Eye problems. Your healthcare provider may send you to an eye care professional to check your eyes if you develop eye problems. Tell your healthcare provider right away if you develop any new or worsening eye problems or vision changes, including:

- blurred vision
- dry eyes
- sensitivity to light

- eye pain or swelling
- eye redness

- Infusion-related reactions. EMRELIS can cause infusion reactions that can be severe or life-threatening. Tell your healthcare provider right away if you develop any signs and symptoms of infusion reactions, including:

- itching or rash
- shortness of breath or wheezing
- flushing
- chest discomfort
- fever

- back pain
- chills
- headache
- nausea or vomiting
- feel like passing out

Getting medical treatment right away may help keep these problems from becoming more serious. Your healthcare provider will check you for these problems during your treatment with EMRELIS and may provide treatment for your side effects. Your healthcare provider may also need to change your dose, temporarily stop, or completely stop treatment with EMRELIS if you have severe side effects.
See “What are the possible side effects of EMRELIS?” for more information about side effects.

What is EMRELIS?
EMRELIS is a prescription medicine used to treat adults with non-squamous non-small cell lung cancer (NSCLC):

- that has spread to areas near the lungs (locally advanced) or to other parts of the body (metastatic), and
- whose tumors have high c-Met protein overexpression, and
- who have received a prior treatment.

Your healthcare provider will perform a test to make sure EMRELIS is right for you.
It is not known if EMRELIS is safe and effective in children.

Before receiving EMRELIS, tell your healthcare provider about all of your medical conditions, including if you:

- have a history of nerve problems
- have lung or breathing problems other than your lung cancer
- have eye problems
- have liver problems
- are pregnant or plan to become pregnant. EMRELIS can harm your unborn baby.

Females who are able to become pregnant:

- Your healthcare provider should do a pregnancy test before you start treatment with EMRELIS.
- You should use effective birth control (contraception) during treatment and for 2 months after your last dose of EMRELIS.
- Tell your healthcare provider if you become pregnant or think that you may be pregnant during treatment with EMRELIS.

Males with female partners who are able to become pregnant:

- You should use an effective birth control during treatment and for 4 months after your last dose of EMRELIS.

- are breastfeeding or plan to breastfeed. It is not known if EMRELIS passes into your breast milk. Do not breastfeed during treatment with EMRELIS and for 1 month after the last dose.

Tell your healthcare provider about all the medicines you take, including prescription and over-the-counter medicines, vitamins, and herbal supplements. Taking certain medicines with EMRELIS may increase your risk of side effects.

How will I receive EMRELIS?

- Your healthcare provider will give you EMRELIS into your vein through an intravenous (IV) line over 30 minutes.
- EMRELIS is given 1 time every 2 weeks.
- Your healthcare provider will decide how many infusions of EMRELIS you will receive.

What are the possible side effects of EMRELIS?
EMRELIS can cause serious side effects, including:

- See “What is the most important information I should know about EMRELIS?”

The most common side effects of EMRELIS include:

- feeling tired

- swelling in the feet, ankles, legs or hands

- decreased appetite

The most common severe abnormal laboratory test results with EMRELIS include:

- decreased white blood cell counts
- increased blood sugar levels
- increased blood liver enzyme levels
- decreased blood phosphorus levels

- decreased blood sodium levels
- decreased red blood cell counts
- decreased blood calcium levels

EMRELIS may cause fertility problems in females and males, which may affect the ability to have children. Talk to your healthcare provider if you have concerns about fertility.
These are not all the possible side effects of EMRELIS.
Call your doctor for medical advice about side effects. You may report side effects to FDA at 1-800-FDA-1088.

General information about the safe and effective use of EMRELIS.
Medicines are sometimes prescribed for purposes other than those listed in a Medication Guide. You can ask your pharmacist or healthcare provider for information about EMRELIS that is written for healthcare professionals.

What are the ingredients in EMRELIS?
Active ingredient: telisotuzumab vedotin-tllv
Inactive ingredients: histidine, polysorbate 80, sucrose. Hydrochloric acid added to adjust the pH.
Manufactured by: AbbVie Inc., North Chicago, IL 60064, USA
U.S. License Number: 1889
Marketed by: AbbVie Inc., North Chicago, IL 60064 U.S.A.
©2025 AbbVie. All rights reserved.
EMRELIS and its design are trademarks of AbbVie Inc.
For more information, go to www.EMRELIS.com or call 1-844-859-5760.

This Medication Guide has been approved by the U.S. Food and Drug Administration. Issued: 05/2025

20090524

PRINCIPAL DISPLAY PANEL

NDC 0074-1044-01

Emrelis™

(telisotuzumab vedotin-tllv)

For Injection

20 mg per vial

Hazardous Drug

For Intravenous Infusion after reconstitution

and dilution

Single-Dose Vial

Discard Unused Portion

Dispense the enclosed Medication Guide to

each patient

Rx Only

abbvie

PRINCIPAL DISPLAY PANEL

NDC 0074-1055-01

Emrelis™

(telisotuzumab vedotin-tllv)

For Injection

100 mg per vial

Hazardous Drug

For Intravenous Infusion after reconstitution

and dilution

Single-Dose Vial

Discard Unused Portion

Dispense the enclosed Medication Guide to

each patient

Rx Only

abbvie